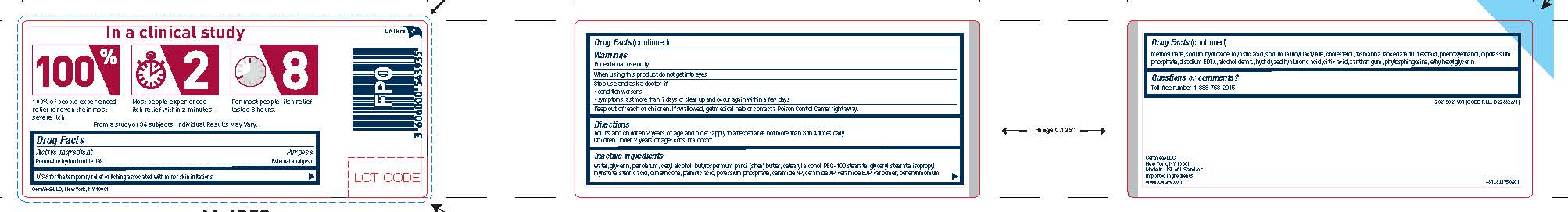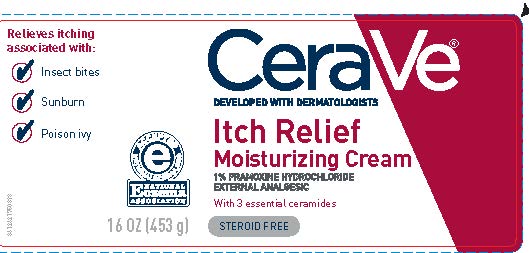 DRUG LABEL: CeraVe Developed with Dermatologists Itch Relief Moisturizing
NDC: 49967-512 | Form: CREAM
Manufacturer: L'Oreal USA Products Inc
Category: otc | Type: HUMAN OTC DRUG LABEL
Date: 20231231

ACTIVE INGREDIENTS: PRAMOXINE HYDROCHLORIDE 10 mg/1 g
INACTIVE INGREDIENTS: WATER; GLYCERIN; PETROLATUM; CETYL ALCOHOL; STEARIC ACID; SHEA BUTTER; CETOSTEARYL ALCOHOL; ISOPROPYL MYRISTATE; GLYCERYL MONOSTEARATE; PEG-100 STEARATE; DIMETHICONE; PALMITIC ACID; MYRISTIC ACID; CERAMIDE 3; CERAMIDE 6 II; CERAMIDE 1; PHENOXYETHANOL; BEHENTRIMONIUM METHOSULFATE; XANTHAN GUM; SODIUM HYDROXIDE; ALCOHOL; ETHYLHEXYLGLYCERIN; SODIUM LAUROYL LACTYLATE; EDETATE DISODIUM; POTASSIUM PHOSPHATE, MONOBASIC; POTASSIUM PHOSPHATE, DIBASIC; TASMANNIA LANCEOLATA FRUIT; PHYTOSPHINGOSINE; CHOLESTEROL; HYALURONIC ACID; CITRIC ACID MONOHYDRATE; CARBOMER HOMOPOLYMER TYPE A (ALLYL PENTAERYTHRITOL CROSSLINKED)

Drug Facts

Active ingredient

Pramoxine hydrochloride 1%

Purpose

External analgesic

Use

For the temporary relief of itching associated with minor skin irritations.

Warnings

For external use only

When using this product

do not get into eyes

Stop use and ask a doctor if

- condition worsens
- symptoms last more than 7 days or clear up and occur again within a few days

Do not use on

- deep or puncture wounds
- animal bites
- serious burns

Keep out of reach of children.

If swallowed, get medical help or contact a Poison Control Center immediately.

Directions

Adults and children 2 years of age and older: apply to affected area not more than 3 to 4 times daily

Children under 2 years of age: consult a doctor.

Inactive ingredients

water, glycerin, petrolatum, cetyl alcohol, butyrospermum parkii (shea) butter, cetearyl alcohol, PEG-100 stearate, glyceryl stearate, isopropyl myristate, stearic acid, dimethicone, palmitic acid, potassium phosphate, ceramide NP, ceramide AP, ceramide EOP, carbomer, behentrimonium methosulfate, sodium hydroxide, myristic acid, sodium lauroyl lactylate, cholesterol, tasmannia lanceolata fruit extract, phenoxyethanol, dipotassium phosphate, disodium EDTA, alcohol denat., hydrolyzed hyaluronic acid, citric acid, xanthan gum, hytosphingosine, ethylhexylglycerin

Questions or comments?

Toll-Free Number 888-768-2915